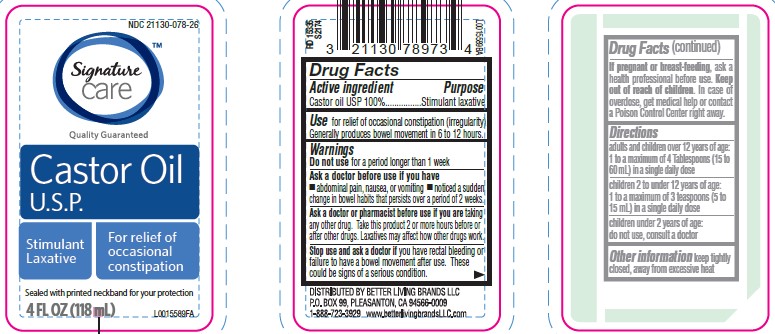 DRUG LABEL: Signature Care
NDC: 21130-078 | Form: OIL
Manufacturer: Better Living Brands, LLC
Category: otc | Type: HUMAN OTC DRUG LABEL
Date: 20260223

ACTIVE INGREDIENTS: CASTOR OIL 1 g/1 mL

Signature Care 078.000/078AA
Castor Oil

Active ingredient

Castor oil USP 100%

Purpose

Stimulant Laxative

Use

For relief of occasional constipation (irregularity). Generally produces bowel movement in 6 to 12 hours.

Warnings

for this product

Do not use

for a period longer than 1 week

Ask a doctor before use if you have

- abdominal pain, nausea, or vomiting
- noticed a sudden change in bowel habits that persists over a period of 2 weeks

Ask a doctor or pharmacist before use if you are

taking any other drug. Take this product 2 or more hours before or after other drugs. Laxatives may affect how other drugs work.

Stop use and ask a doctor

if you have rectal bleeding or failure to have a bowel movement after use. These could be signs of a serious condition.

If pregnant or breast-feeding,

ask a health professional before use.

Keep out of reach of children.

In case of overdose, get medical help or contact a Poison Control Center right away.

Directions

Adults and children over 12 years of age - 1 to a maximum of 4 tablespoons (15 to 60 mL) in a single daily dose

children 2 to under 12 years of age - 1 to a maximum of 3 teaspoons (5 to 15 mL) in a single daily dose

children under 2 years of age - do not use, consult a doctor

Inactive Ingredient

None

Other information

Keep tightly closed, away from excessive heat.

ADVERSE REACTION

DISTRIBUTED BY BETTER LIVING BRANDS LLC

PO. BOX 99, PLEASANTON, CA 94566-0009

1-888-723-3929 www.betterlivingbrandsLLC.com

principal display panel

NDC 21130-078-26

Signature Care™

Quality Guaranteed

Castor Oil U.S.P.

Stimulant Laxative

For relief of occasional constipation

Sealed with printed neckband for your protection

4 FL OZ (118 mL)